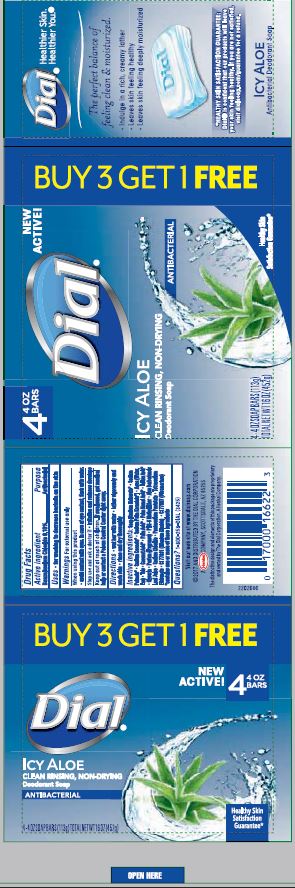 DRUG LABEL: Dial Antibacterial Bar
NDC: 54340-271 | Form: SOAP
Manufacturer: The Dial Corporation, A Henkel Company
Category: otc | Type: HUMAN OTC DRUG LABEL
Date: 20170811

ACTIVE INGREDIENTS: BENZALKONIUM CHLORIDE 0.1 g/100 g
INACTIVE INGREDIENTS: SODIUM TALLOWATE, BEEF 59.1 g/100 g

Dial Icy Aloe

Active Ingredient

Benzalkonium Chloride 0.1%

Purpose

Antibacterial

Uses

For washing to decrease the bacteria on the skin.

Warning

For external use only.

When using this product avoid contact with eyes. In case of eye contact, flush with water.

Stop using and ask doctor if irritation or redness develops.

Keep out of reach of children

If swallowed, get medical help or contact Poison Control Center right away.

Directions

wet bar with water

lather vigorously and wash skin

rinse and dry thoroughly

Inactive Ingredients

Soap [Sodium Tallowate*, Sodium Palmate*, Sodium Cocoate*, Sodium Palm Kernelate*], Aqua (Water, Eau), Talc, Coconut Acid*, Palm Acid*, Palm Kernel Acid*, Tallow Acid*, Glycerin, Parfum (Fragrance), PEG-6 Methyl Ether, Aloe Barbadensis Leaf Juice, Sodium Chloride, Pentasodium Pentetate, Tetrasodium Etidronate, CI 77891 (Titanium Dioxide), CI 77007 (Ultramarines) *Contains one or more of these ingredients

Questions 1 800 258 DIAL

Visit our website at www.dialsoap.com

2017 AND DISTRIBUTED BY THE DIAL CORPORATION

A HENKEL COMPANY, SCOTTSDALE, AZ 85255

The distinctive design and elements of this package are proprietary and owned by The Dial Corporation, A Henkel Company.